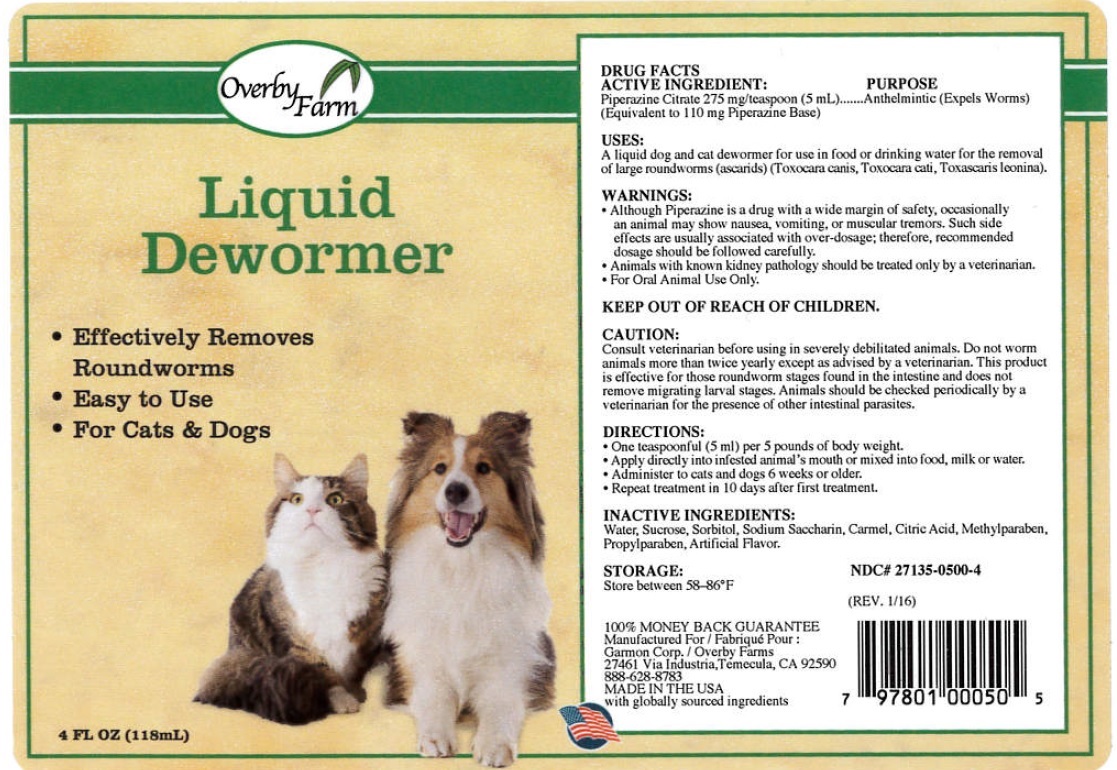 DRUG LABEL: Liquid Dewormer
NDC: 27135-0500 | Form: LIQUID
Manufacturer: The Garmon Corporation
Category: animal | Type: OTC ANIMAL DRUG LABEL
Date: 20170508

ACTIVE INGREDIENTS: PIPERAZINE CITRATE 275 mg/5 mL
INACTIVE INGREDIENTS: WATER; SUCROSE; SORBITOL; SACCHARIN SODIUM; CITRIC ACID MONOHYDRATE; METHYLPARABEN; PROPYLPARABEN

Overby Farm Liquid Dewormer

Product Facts

Piperazine Citrate 275 mg/teaspoon (5 mL)…....Anthelmintic (Expels Worms)
(Equivalent to 110 mg Piperazine Base)

USES:
■ A liquid dog and cat wormer for use in food or drinking water for the
removal of large roundworms (ascarids) (Toxocara canis, Toxocara cati,
Toxascaris leonina).

WARNINGS:
■ Although Piperazine is a drug with a wide margin of safety. Occasionally
an animal may show nausea, vomiting, or muscular tremors. Such side
effects are usually associated with over-dosage: Therefore, recommended
dosage should be followed carefully.
■ Animals with known kidney pathology should be treated only by
a veterinarian.
■ For Oral Animal Use Only.

KEEP OUT OF REACH OF CHILDREN.

PRECAUTIONS

CAUTION:

Consult veterinarian before using in severely debilitated
animals. Do not worm animals more than twice yearly except as advised by
a veterinarian. This product is effective for those roundworm stages found
in the intestine and does not remove migrating larval stages. Animals
should be checked periodically by a veterinarian or the presence of other
intestinal parasites.

DIRECTIONS:
■ One teaspoonful (5 ml) per 5 pounds of body weight.
■ Applied directly into infested animal mouth or mixed into food, milk or water.
■ Administer to cats and dogs 6 weeks or older.
■ Repeat treatment in 10 days after first treatment.

INACTIVE INGREDIENTS: Water, Sucrose, Sorbitol, Sodium Saccharin,
Carmel, Citric Acid, Methylparaben, Propylparaben, Artificial Flavor.

STORAGE: Store between 58 – 86°F